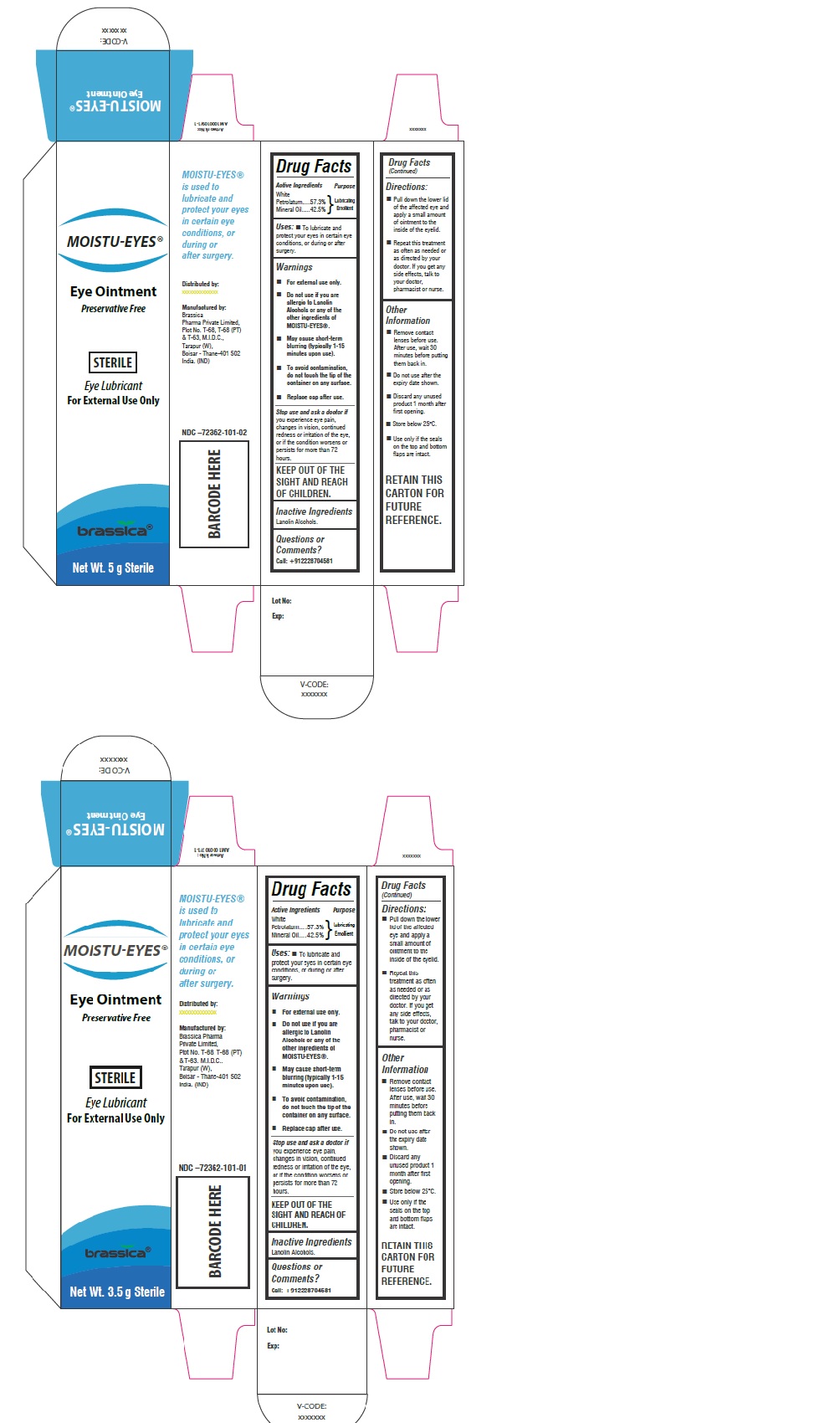 DRUG LABEL: MOISTU-EYES
NDC: 72362-101 | Form: OINTMENT
Manufacturer: BRASSICA PHARMA PRIVATE LIMITED
Category: otc | Type: HUMAN OTC DRUG LABEL
Date: 20200128

ACTIVE INGREDIENTS: PETROLATUM 57.3 g/100 g; MINERAL OIL 42.5 g/100 g
INACTIVE INGREDIENTS: LANOLIN ALCOHOLS

MOISTU-EYES®

Ingredients:

White Petrolatum 57.3%

Mineral Oil 42.5%

Purpose

Lubricating Emollient

Uses:

- To lubricate and protect your eyes in certain eye conditions, or during or after surgery.

Warning

- For external use only.
- Do not use if you are allergic to Lanolin Alcohols or any of the other ingredients of MOISTU-EYES®.
- May cause short-term blurring (typically 1-15 minutes upon use).

Do not drive or use machinery unless your vision is clear.

Stop use and ask a doctor if

you experience any of the following, stop use and see your doctor: eye pain, eye irritation, eye redness, eye itching, swelling of the eyelid, increased tear production, feeling there's something in your eye, hypersensitivity (allergic reaction).

Keep out of reach and sight of children.

Directions:

- Pull lower lid down to form a pouch and apply a small strip of ointment to it.
- Repeat this treatment as often as needed or as directed by your doctor. If you get any side effects, talk to your doctor, pharmacist or nurse.

Other Information

- Remove contact lenses before use. After use, wait 30 minutes before putting them back in.
- Do not use after the expiry date shown.
- Discard any unused product 1 month after first opening.
- Store below 25°C.

Inactive Ingredients:

Lanolin Alcohols.

Question or Comments:

Call: +912228704581

Eye Ointment
Preservative Free

STERILE

Eye Lubricant
For External Use

Moistueyes® is used to lubricate and protect your eyes in certain eye conditions, or during or after surgery.

Distributed by:
Amilco Ltd, Mckenzie House, Bury Street, Ruislip, HA4 7TL, UK

Manufactured by:
Brassica Pharma Private Limited,
Plot No.T-68, T-68 (PT) & T-63, M.I.D.C., Tarapur, (W), Boisar - Thane-401 502 India. (IND)